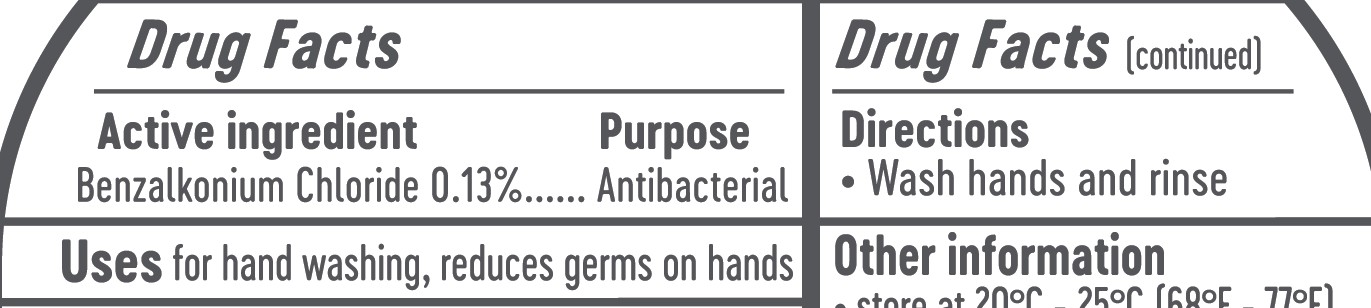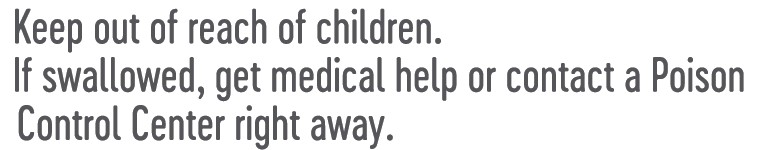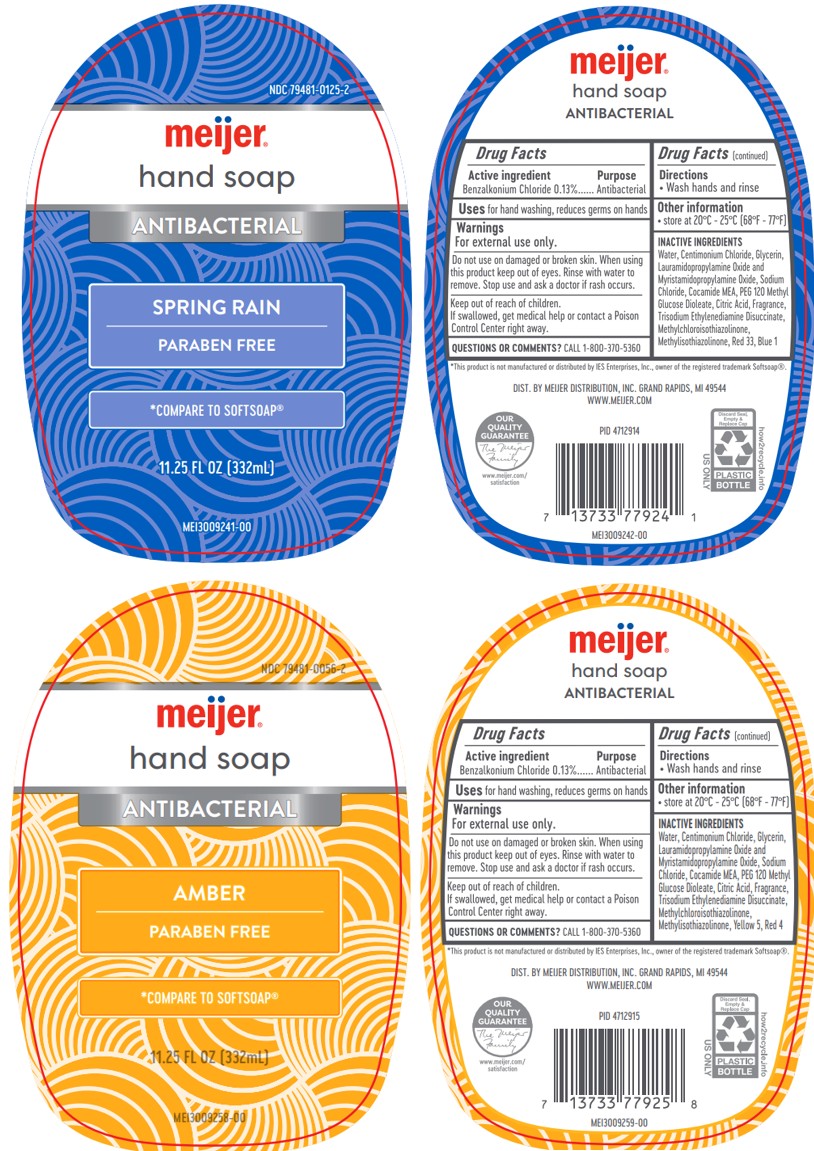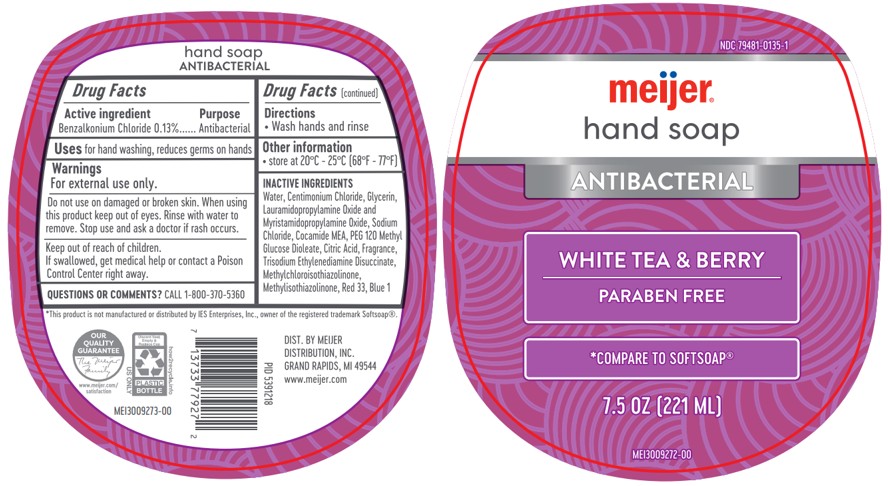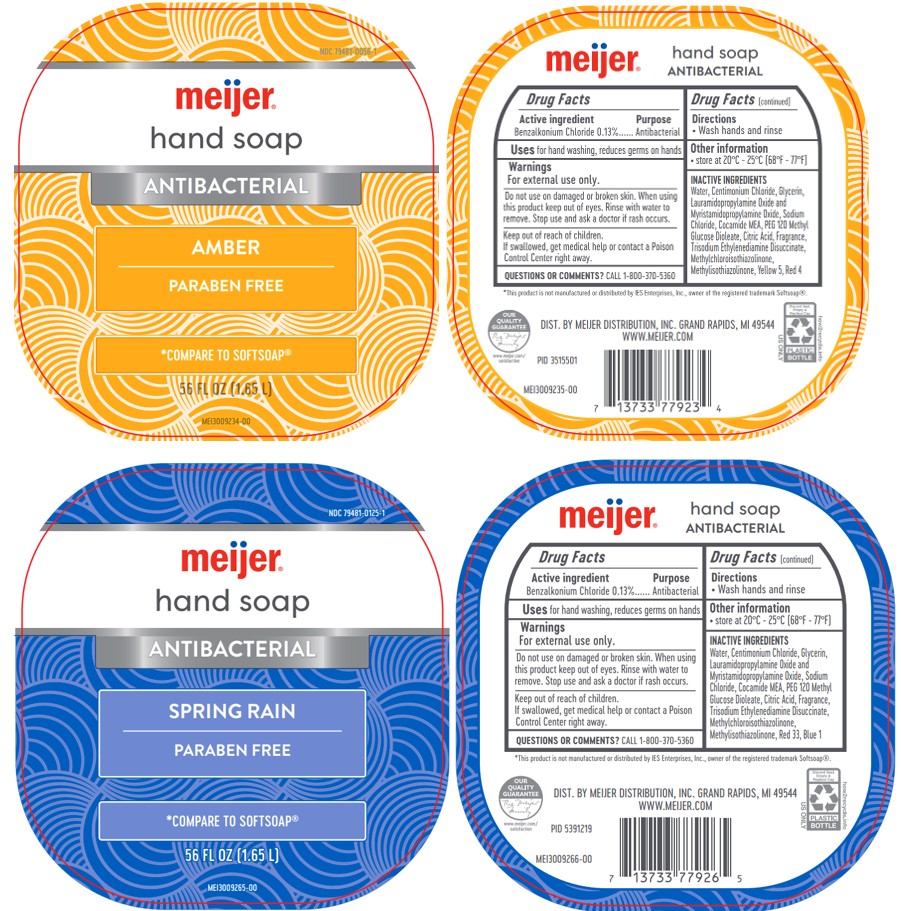 DRUG LABEL: Meijer Antibacterial Spring Rain Hand
NDC: 79481-0125 | Form: SOAP
Manufacturer: Meijer, Inc.
Category: otc | Type: HUMAN OTC DRUG LABEL
Date: 20241205

ACTIVE INGREDIENTS: BENZALKONIUM CHLORIDE 0.13 g/100 mL
INACTIVE INGREDIENTS: WATER; CETRIMONIUM CHLORIDE; GLYCERIN; LAURAMIDOPROPYLAMINE OXIDE; MYRISTAMIDOPROPYLAMINE OXIDE; SODIUM CHLORIDE; COCAMIDE MEA; CITRIC ACID; TRISODIUM ETHYLENEDIAMINE DISUCCINATE; METHYLCHLOROISOTHIAZOLINONE; METHYLISOTHIAZOLINONE; FD&C BLUE NO. 1; RED 33; PEG-120 METHYL GLUCOSE DIOLEATE

Meijer® Antibacterial Hand Soap

Warnings

For external use only

Do not use on damaged or broken skin. When using this product keep out of eyes. Rinse with water to remove. Stop use and ask a doctor if rash occurs.

Keep out of reach of children.

If swallowed, get medical help or contact a Poison Control Center right away.

Activce Ingredient

Active Ingredient Purpose

Benzalkonium Chloride 0.13%......Antibacterial

Antibacterial

Directions

Wash hands and rinse

Adverse event reporting

QUESTIONS OR COMMENTS? CALL 1-800-370-5360

Dosage and Administration

Apply 1-2 pumps to hands rub and rinse to reduce the amount of bacteria on hands

Inactive Ingredients

Water, Centimonium Chloride, Glycerin, Lauramidopropylamine Oxide and Myristamidopropylamine Oxide, Sodium Chloride, Cocamide MEA, PEG 120 Methyl Glucose Dioleate, Citric Acid, Fragrance, Trisodium Ethylenediamine Disuccinate, Methylchloroisothiazolinone, Methylisothiazolinone

Amber: Yellow 5, Red 4

Spring Rain: Red 33, Blue 1

White Tea and Berry: Red 33, Blue 1

Other information: Storage

Avoid extreme temperatures: store at 20-25C (68-77F)

Keep out of reach of children

If swallowed, get medical help or contact a Poison Contol Center right away

Meijer Antibacterial Hand Soap